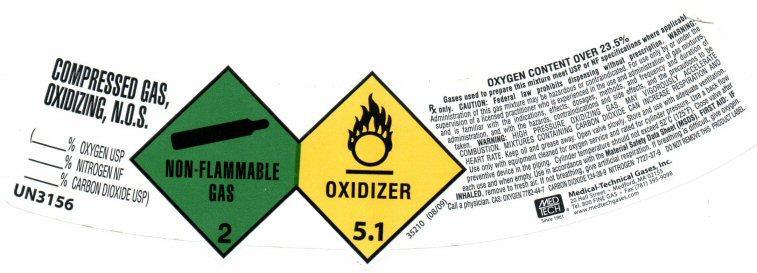 DRUG LABEL: COMPRESSED GAS, OXIDIZING, N.O.S.
NDC: 10736-009 | Form: GAS
Manufacturer: Medical-Technical Gases, Inc.
Category: prescription | Type: HUMAN PRESCRIPTION DRUG LABEL
Date: 20121222

ACTIVE INGREDIENTS: OXYGEN 95 mL/1 L; CARBON DIOXIDE 5 mL/1 L
INACTIVE INGREDIENTS: NITROGEN

Product Label

COMPRESSED GAS, OXIDIZING, N.O.S.
,
______ % OXYGEN USP,
_______ % NITROGEN NF
_______% CARBON DIOXIDE (USP)

UN 3156 NON-FLAMMABLE GAS 2 OXIDIZER 5.1 35210 (08/09)
OXYGEN CONTENT OVER 23.5%
GASES USED TO PREPARE THIS MIXTURE MEET USP OR NF SPECIFICATIONS WHERE APPLICABLE.
Rx only: CAUTION: Federal law prohibits dispensing without a prescription.
WARNING: Administration of this gas mixture may be hazardous or contraindicated. For use only by or under the supervision of a licensed practitioner who is experienced in the use and administration of gas mixtures, and is familiar with the indications, effects, dosages, methods, and frequency and duration of administration, and with the hazards, contraindications, and side effects and the precautions to be taken.
WARNING: HIGH PRESSURE OXIDIZING GAS. MAY VIGOROUSLY ACCELERATE COMBUSTION. MIXTURES CONTAINING CARBON DIOXIDE CAN INCREASE RESPIRATIONS AND HEART RATE. Keep oil and grease away. Open valve slowly. Store and use with adequate ventilation. Use only with equipment cleaned for oxygen service and rated for cylinder pressure. Use a back flow preventive device in the piping. Cylinder temperature should not exceed 52° C (125° F). Close valve after each use and when empty. Use in accordance with the Material Safety Data Sheet (MSDS).FIRST AID: IF INHALED, remove to fresh air. If not breathing, give artificial respiration. If breathing is difficult, give oxygen. Call a physician.
CAS: OXYGEN 7782-44-7 CARBON DIOXIDE: 124-38-9 NITROGEN: 7727-37-9 DO NOT REMOVE THIS PRODUCT LABEL
MEDTECH Since 1961
Medical-Technical Gases, Inc.
20 Hall Street, Medford, MA 02155
Tel. 800 FINE GAS FAX (781)-395-9098
www.medtechgases.com